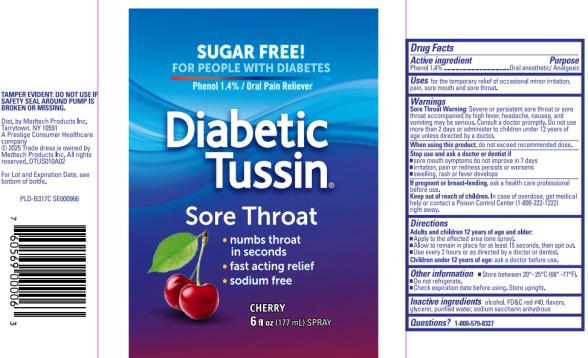 DRUG LABEL: Diabetic Tussin Sore Throat Cherry
NDC: 61787-066 | Form: SPRAY
Manufacturer: MEDTECH PRODUCTS INC
Category: otc | Type: HUMAN OTC DRUG LABEL
Date: 20251023

ACTIVE INGREDIENTS: PHENOL 1.4 mg/1 mL
INACTIVE INGREDIENTS: ALCOHOL; FD&C RED NO. 40; GLYCERIN; WATER; SACCHARIN SODIUM ANHYDROUS

Diabetic Tussin Sore Throat Cherry Spray

Drug Facts

Active ingredient

Phenol 1.4%

Purpose

Oral anesthetic/Analgesic

Uses

for the temporary relief of occasional minor irritation, pain, sore mouth and sore throat.

Warnings

Sore Throat Warning: Severe or persistent sore throat or sore throat accompanied by high fever, headache, nausea, and vomiting may be serious.

Consult a doctor promptly. Do not use more than 2 days or administer to children under 12 years of age unless directed by a doctor.

When using this product,

do not exceed recommended dose.

Stop use and ask a doctor or dentist if

- sore mouth symptoms do not improve in 7 days
- irritation, pain or redness persists or worsens
- swelling, rash or fever develops

If pregnant or breast-feeding,

ask a health care professional before use.

Keep out of reach of children.

In case of overdose, get medical help or contact a Poison Control Center (1-800-222-1222) right away.

Directions

Adults and children 12 years of age and older:

- Apply to the affected area (one spray).
- Allow to remain in place for at least 15 seconds, then spit out.
- Use every 2 hours or as directed by a doctor or dentist.

Children under 12 years of age: ask a doctor before use.

Other information

- store between 20°-25°C (68-°77°F).
- do not refrigerate.
- Check expiration date before using. Store upright.

Inactive ingredients

alcohol, FD&C red #40, flavors, glycerin, purified water, sodium saccharin anhydrous

Questions?

1-800-579-8327

Principal Display Panel

Diabetic Tussin®
Phenol / Oral Pain Reliever
Cherry
6 fl oz (177 mL) SPRAY